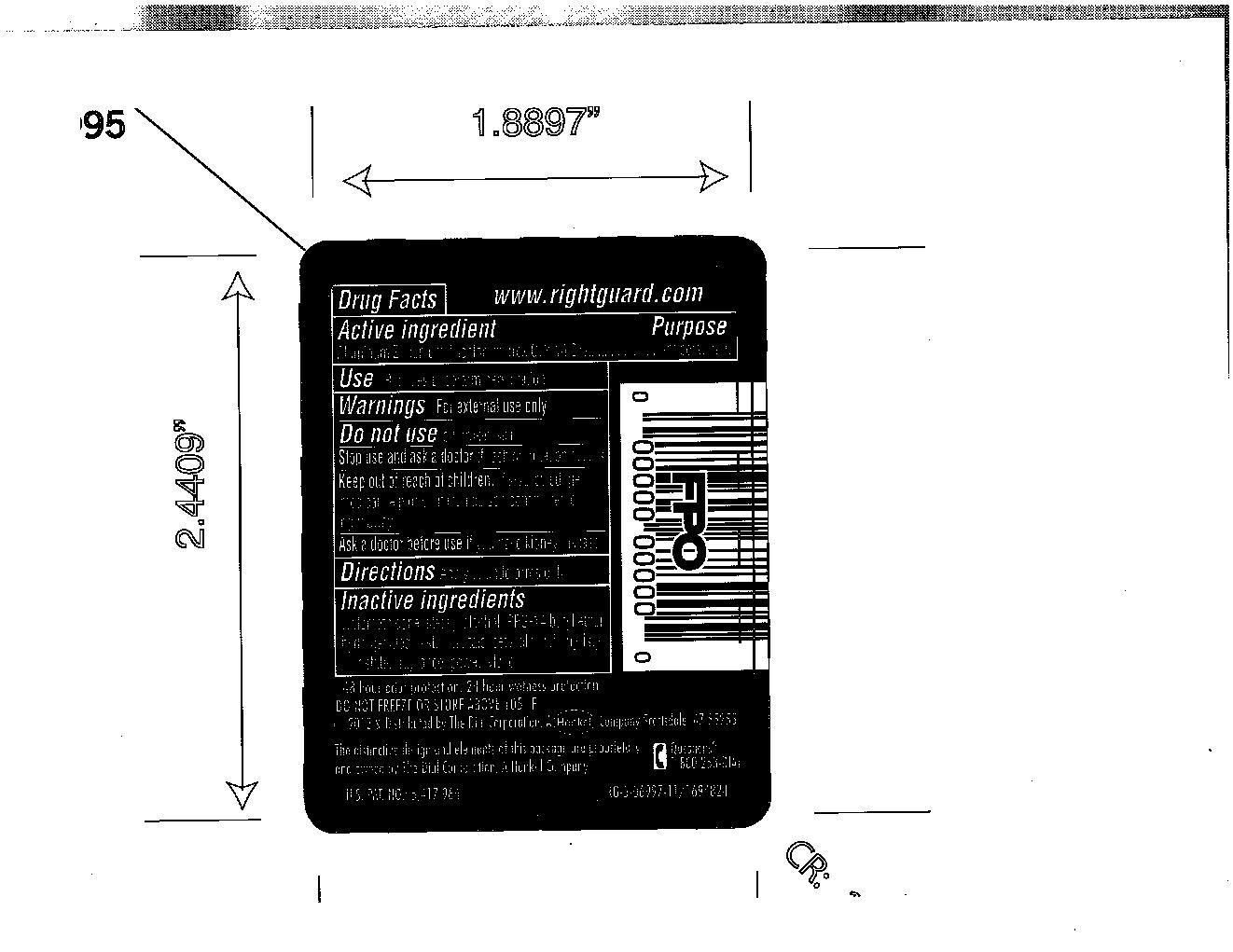 DRUG LABEL: Right Guard Sport
NDC: 51815-225 | Form: STICK
Manufacturer: VVF Illinois Services
Category: otc | Type: HUMAN OTC DRUG LABEL
Date: 20140403

ACTIVE INGREDIENTS: ALUMINUM ZIRCONIUM TRICHLOROHYDREX GLY 7.14 g/51 g
INACTIVE INGREDIENTS: CYCLOMETHICONE; STEARYL ALCOHOL; PPG-14 BUTYL ETHER; HYDROGENATED CASTOR OIL; TALC; CETYL ALCOHOL; MYRISTYL MYRISTATE; POLYETHYLENE GLYCOL 400

Right Guard Sport Triathlon

Active Ingredient

Aluminum Zirconium Trichlorohydrex GLY 14.0%

Purpose

Antiperspirant

Warnings

For external use only

Stop use and ask a doctor if rash or irritation occurs

Keep out of reach of children

If swallowed, get medical help or contact a poison control center right away.

Use

Reduces underarm perspiration

Ask a doctor before use if you have kidney disease

Inactive ingredients

cyclomethicone, stearyl alcohol, PPG-14 butyl ether, hydrogenated castor oil, talc, cetyl alcohol, myristyl myristate, fragrance, polythylene.

QUESTIONS

Call 1-800-258-DIAL

Directions

Apply to underarms only.